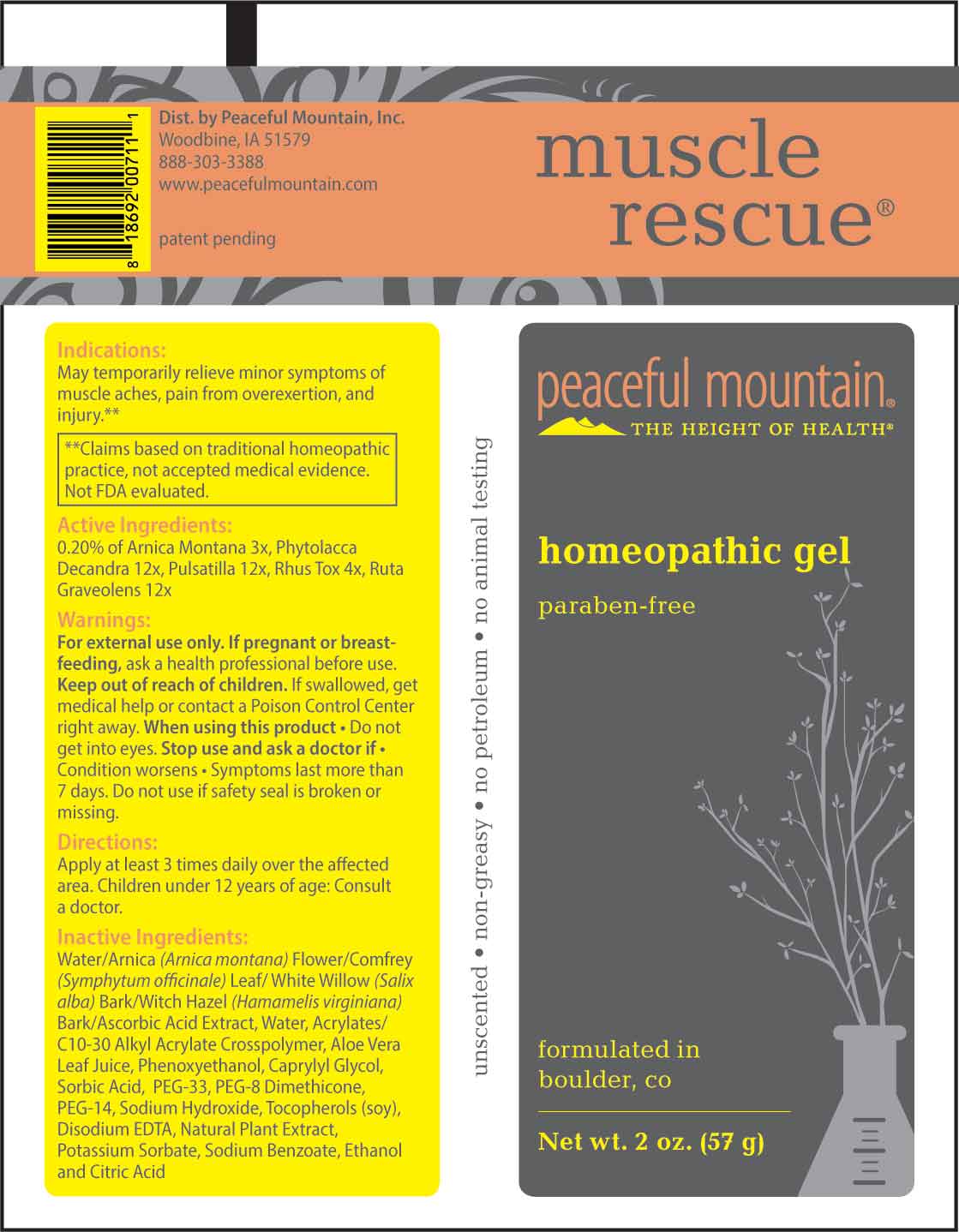 DRUG LABEL: MUSCLE RESCUE
NDC: 43846-0083 | Form: GEL
Manufacturer: Peaceful Mountain, Inc.
Category: homeopathic | Type: HUMAN OTC DRUG LABEL
Date: 20240611

ACTIVE INGREDIENTS: ARNICA MONTANA WHOLE 3 [hp_X]/1 g; TOXICODENDRON PUBESCENS LEAF 4 [hp_X]/1 g; PHYTOLACCA AMERICANA ROOT 12 [hp_X]/1 g; PULSATILLA VULGARIS WHOLE 12 [hp_X]/1 g; RUTA GRAVEOLENS FLOWERING TOP 12 [hp_X]/1 g
INACTIVE INGREDIENTS: WATER; PHENOXYETHANOL; CAPRYLYL GLYCOL; SORBIC ACID; SODIUM HYDROXIDE; CARBOMER COPOLYMER TYPE A (ALLYL PENTAERYTHRITOL CROSSLINKED); POLYETHYLENE GLYCOL 1600; PEG-8 DIMETHICONE (600 CST); POLYETHYLENE GLYCOL 700; ALOE VERA LEAF; .ALPHA.-TOCOPHEROL; EDETATE DISODIUM; OREGANO; POTASSIUM SORBATE; ARNICA MONTANA FLOWER; COMFREY LEAF; SALIX ALBA BARK; HAMAMELIS VIRGINIANA BARK; ASCORBIC ACID; SODIUM BENZOATE; ALCOHOL; CITRIC ACID MONOHYDRATE

DRUG FACTS:

ACTIVE INGREDIENTS:

0.20% of Arnica Montana 3X, Phytolacca Decandra 12X, Pulsatilla 12X, Rhus Tox 4X, Ruta Graveolens 12X.

PURPOSE:

May temporarily relieve minor symptoms of muscle aches, pains from overexertion, and injury.**

**Claims based on traditional homeopathic practice, not accepted medical evidence. Not FDA evaluated.

WARNINGS:

For external use only.

If pregnant or breast-feeding, ask a health professional before use.

Keep out of reach of children. If swallowed, get medical help or contact a Poison Control Center right away.

When using this product. Do not get into eyes.

Stop use and ask a doctor if. Condition worsens • Symptoms last more than 7 days. Do not use if safety seal is broken or missing.

KEEP OUT OF REACH OF CHILDREN:

If swallowed, get medical help or contact a Poison Control Center right away.

DIRECTIONS:

Apply at least 3 times daily over the affected area. Children under 12 years of age: Consult a doctor.

INDICATIONS:

May temporarily relieve minor symptoms of muscle aches, pains from overexertion, and injury.**

**Claims based on traditional homeopathic practice, not accepted medical evidence. Not FDA evaluated.

INACTIVE INGREDIENTS:

Water/Arnica (Arnica Montana) Flower/Comfrey (Symphytum officinale) Leaf/White Willow (Salix Alba) Bark/Witch Hazel (Hamamelis Virginiana) Bark/Ascorbic Acid Extract, Water, Acrylates/C10-30 Alkyl Acrylate Crosspolymer, Aloe Vera Leaf Juice, Phenoxyethanol, Caprylyl Glycol, Sorbic Acid, PEG-33, PEG-8 Dimethicone, PEG-14, Sodium Hydroxide, Tocopherols (Soy), Disodium EDTA, Natural Plant Extract, Potassium Sorbate, Sodium Benzoate, Ethanol and Citric Acid

QUESTIONS:

Dist. by Peaceful Mountain, Inc.

Woodbine, IA 51579

888-303-3388

www.peacefulmountain.com

PACKAGE DISPLAY LABEL:

Muscle rescue

Peaceful Mountain

homeopathic gel

Net wt. 2 oz. (57 g)